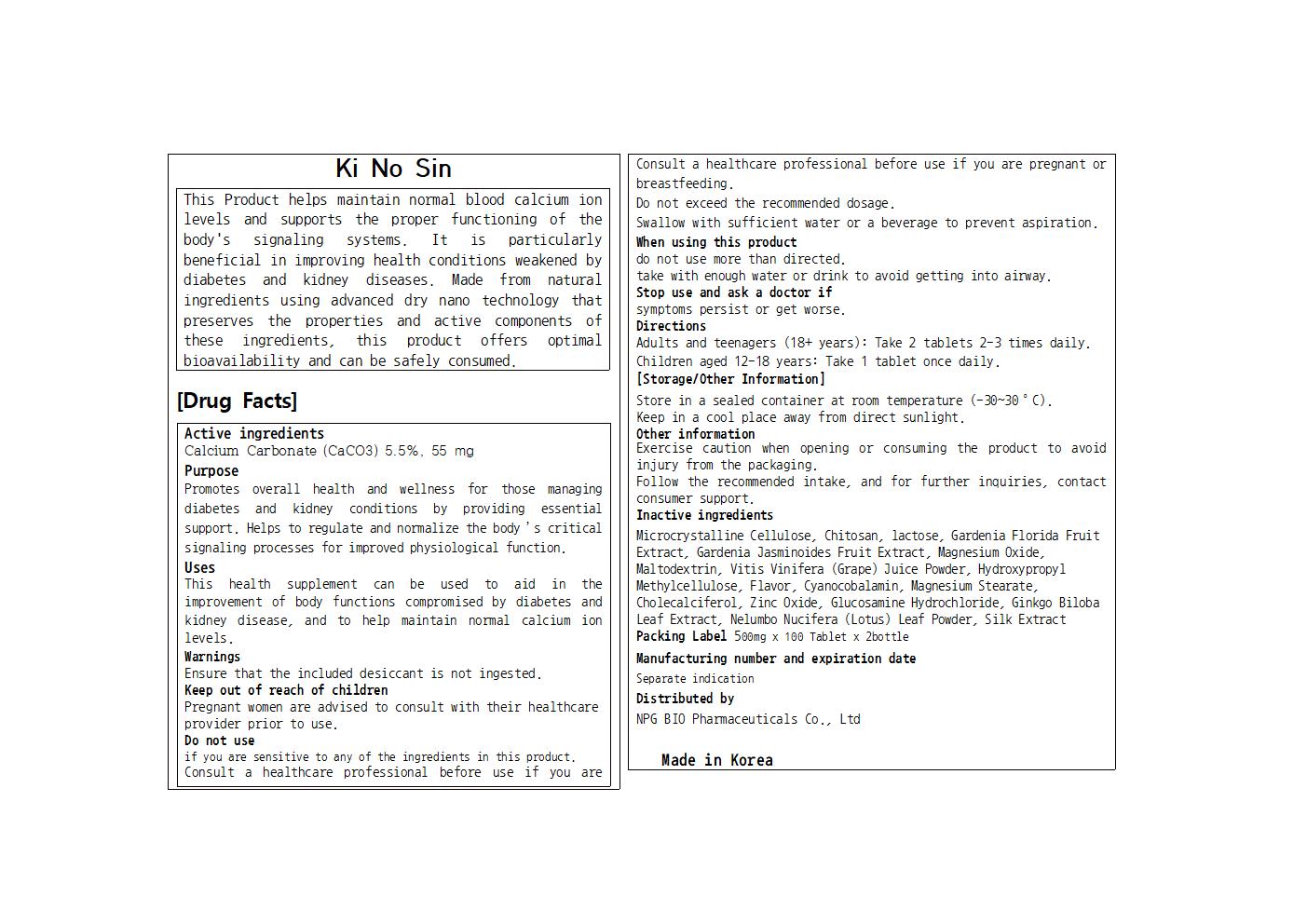 DRUG LABEL: Ki No Sin
NDC: 84540-322 | Form: TABLET
Manufacturer: NPG Bio Pharmaceuticals Co.,Ltd.
Category: otc | Type: HUMAN OTC DRUG LABEL
Date: 20250827

ACTIVE INGREDIENTS: CALCIUM CARBONATE 55 mg/500 mg
INACTIVE INGREDIENTS: LACTOSE, UNSPECIFIED FORM; HYPROMELLOSES; ZINC OXIDE; WINE GRAPE JUICE; GARDENIA JASMINOIDES FRUIT; CHOLECALCIFEROL; MAGNESIUM STEARATE; GLUCOSAMINE HYDROCHLORIDE; GINKGO; BOMBYX MORI FIBER; NELUMBO NUCIFERA LEAF; MALTODEXTRIN; MAGNESIUM OXIDE; POLIGLUSAM; CYANOCOBALAMIN; MICROCRYSTALLINE CELLULOSE

84540-322 Ki No Sin PTP

Active Ingredients

Calcium Carbonate (CaCO3) 5.5%, 55 mg

Purposes

Promotes overall health and wellness for those managing diabetes and kidney conditions by providing essential support. Helps to regulate and normalize the body’s critical signaling processes for improved physiological function.

Uses

This health supplement can be used to aid in the improvement of body functions compromised by diabetes and kidney disease, and to help maintain normal calcium ion levels.

Warnings

if you are sensitive to any of the ingredients in this product.

Consult a healthcare professional before use if you are pregnant or breastfeeding.

Do not exceed the recommended dosage.

Swallow with sufficient water or a beverage to prevent aspiration.

Warnings

Keep out of reach of children

Pregnant women are advised to consult with their healthcare provider prior to use.

Warnings

Stop use and ask a doctor if

symptoms persist or get worse.

Warnings

When using this product

do not use more than directed.

take with enough water or drink to avoid getting into airway.

Warnings

Ensure that the included desiccant is not ingested.

Directions

Adults and teenagers (18+ years): Take 2 tablets 2-3 times daily.

Children aged 12-18 years: Take 1 tablet once daily.

Inactive Ingredients

Microcrystalline Cellulose, Chitosan, lactose, Gardenia Florida Fruit Extract, Gardenia Jasminoides Fruit Extract, Magnesium Oxide, Maltodextrin, Vitis Vinifera (Grape) Juice Powder, Hydroxypropyl Methylcellulose, Flavor, Cyanocobalamin, Magnesium Stearate, Cholecalciferol, Zinc Oxide, Glucosamine Hydrochloride, Ginkgo Biloba Leaf Extract, Nelumbo Nucifera (Lotus) Leaf Powder, Silk Extract